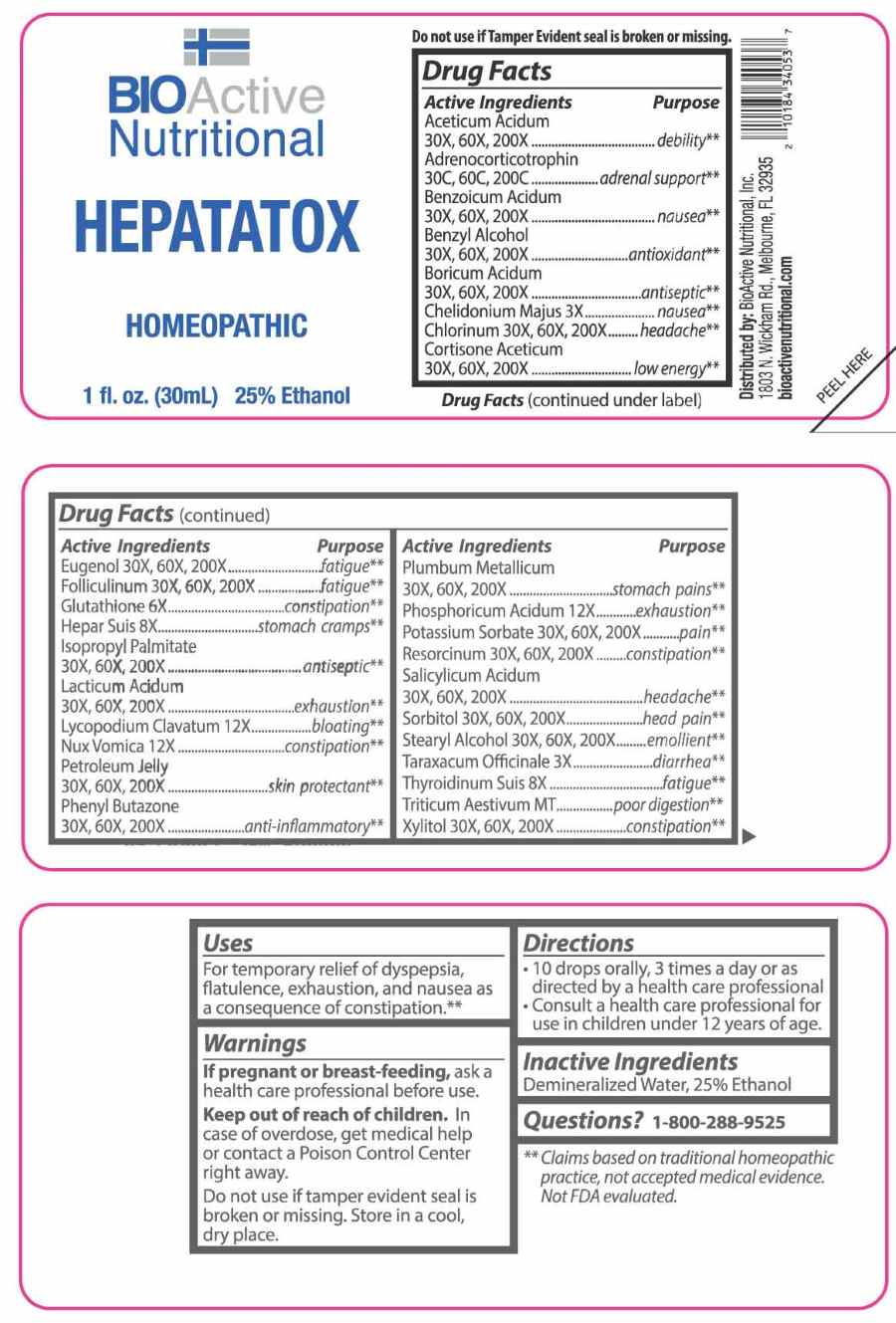 DRUG LABEL: Hepatatox
NDC: 43857-0543 | Form: LIQUID
Manufacturer: BioActive Nutritional, Inc
Category: homeopathic | Type: HUMAN OTC DRUG LABEL
Date: 20251218

ACTIVE INGREDIENTS: TRITICUM AESTIVUM WHOLE 1 [hp_X]/1 mL; CHELIDONIUM MAJUS WHOLE 3 [hp_X]/1 mL; TARAXACUM OFFICINALE 3 [hp_X]/1 mL; GLUTATHIONE 6 [hp_X]/1 mL; PORK LIVER 8 [hp_X]/1 mL; THYROID 8 [hp_X]/1 mL; LYCOPODIUM CLAVATUM SPORE 12 [hp_X]/1 mL; STRYCHNOS NUX-VOMICA SEED 12 [hp_X]/1 mL; PHOSPHORIC ACID 12 [hp_X]/1 mL; CORTICOTROPIN 30 [hp_C]/1 mL; SALICYLIC ACID 30 [hp_X]/1 mL; CORTISONE ACETATE 30 [hp_X]/1 mL; EUGENOL 30 [hp_X]/1 mL; STEARYL ALCOHOL 30 [hp_X]/1 mL; XYLITOL 30 [hp_X]/1 mL; ESTRONE 30 [hp_X]/1 mL; BENZOIC ACID 30 [hp_X]/1 mL; CHLORINE 30 [hp_X]/1 mL; POTASSIUM SORBATE 30 [hp_X]/1 mL; SORBITOL 30 [hp_X]/1 mL; RESORCINOL 30 [hp_X]/1 mL; BENZYL ALCOHOL 30 [hp_X]/1 mL; LACTIC ACID, DL- 30 [hp_X]/1 mL; ISOPROPYL PALMITATE 30 [hp_X]/1 mL; BORIC ACID 30 [hp_X]/1 mL; ACETIC ACID 30 [hp_X]/1 mL; PHENYLBUTAZONE 30 [hp_X]/1 mL; PETROLATUM 30 [hp_X]/1 mL; LEAD 30 [hp_X]/1 mL
INACTIVE INGREDIENTS: WATER; ALCOHOL

DRUG FACTS:

ACTIVE INGREDIENTS:

Aceticum Acidum 30X, 60X, 200X, Adrenocorticotrophin 30C, 60C, 200C, Benzoicum Acidum 30X, 60X, 200X, Benzyl Alcohol 30X, 60X, 200X, Boricum Acidum 30X, 60X, 200X, Chelidonium Majus 3X, Chlorinum 30X, 60X, 200X, Cortisone Aceticum 30X, 60X, 200X, Eugenol 30X, 60X, 200X, Folliculinum 30X, 60X, 200X, Glutathione 6X, Hepar Suis 8X, Isopropyl Palmitate 30X, 60X, 200X, Lacticum Acidum 30X, 60X, 200X, Lycopodium Clavatum 12X, Nux Vomica 12X, Petroleum Jelly 30X, 60X, 200X, Phenyl Butazone 30X, 60X, 200X, Plumbum Metallicum 30X, 60X, 200X, Phosphoricum Acidum 12X, Potassium Sorbate 30X, 60X, 200X, Resorcinum 30X, 60X, 200X, Salicylicum Acidum 30X, 60X, 200X, Sorbitol 30X, 60X, 200X, Stearyl Alcohol 30X, 60X, 200X, Taraxacum Officinale 3X, Thyroidinum Suis 8X, Triticum Aestivum 1X, Xylitol 30X, 60X, 200X.

PURPOSE:

Aceticum Acidum - debility,** Adrenocorticotrophin – adrenal support,** Benzoicum Acidum - nausea,** Benzyl Alcohol - antioxidant,** Boricum Acidum - antiseptic,** Chelidonium Majus - nausea,** Chlorinum - headache,** Cortisone Aceticum – low energy,** Eugenol - fatigue,** Folliculinum - fatigue,** Glutathione - constipation,** Hepar Suis – stomach cramps,** Isopropyl Palmitate - antiseptic,** Lacticum Acidum - exhaustion,** Lycopodium Clavatum - bloating,** Nux Vomica - constipation,** Petroleum Jelly – skin protectant,** Phenyl Butazone – anti-inflammatory,** Plumbum Metallicum – stomach pains,** Phosphoricum Acidum - exhaustion,** Potassium Sorbate - pain,** Resorcinum - constipation,** Salicylicum Acidum - headache,** Sorbitol – head pain,** Stearyl Alcohol - emollient,** Taraxacum Officinale - diarrhea,** Thyroidinum Suis - fatigue,** Triticum Aestivum – poor digestion,** Xylitol – constipation**

**Claims based on traditional homeopathic practice, not accepted medical evidence. Not FDA evaluated.

USES:

For temporary relief of dyspepsia, flatulence, exhaustion, and nausea as a consequence of constipation.**

**Claims based on traditional homeopathic practice, not accepted medical evidence. Not FDA evaluated.

WARNINGS:

If pregnant or breast-feeding, ask a health care professional before use.

Keep out of reach of children. In case of overdose, get medical help or contact a Poison Control Center right away.

Do not use if tamper evident seal is broken or missing.

Store in a cool, dry place.

KEEP OUT OF REACH OF CHILDREN:

In case of overdose, get medical help or contact a Poison Control Center right away.

DIRECTIONS:

• 10 drops orally, 3 times a day or as directed by a health care professional.

• Consult a health care professional for use in children under 12 years of age.

INACTIVE INGREDIENTS:

Demineralized Water, 25% Ethanol

QUESTIONS:

Distributed by:

BioActive Nutritional, Inc.

1803 N. Wickham Rd.

Melbourne, FL 32935

bioactivenutritional.com

1-800-288-9525

PACKAGE LABEL DISPLAY:

BIOActive Nutritional

HEPATATOX

HOMEOPATHIC

1 fl. oz. (30 mL)